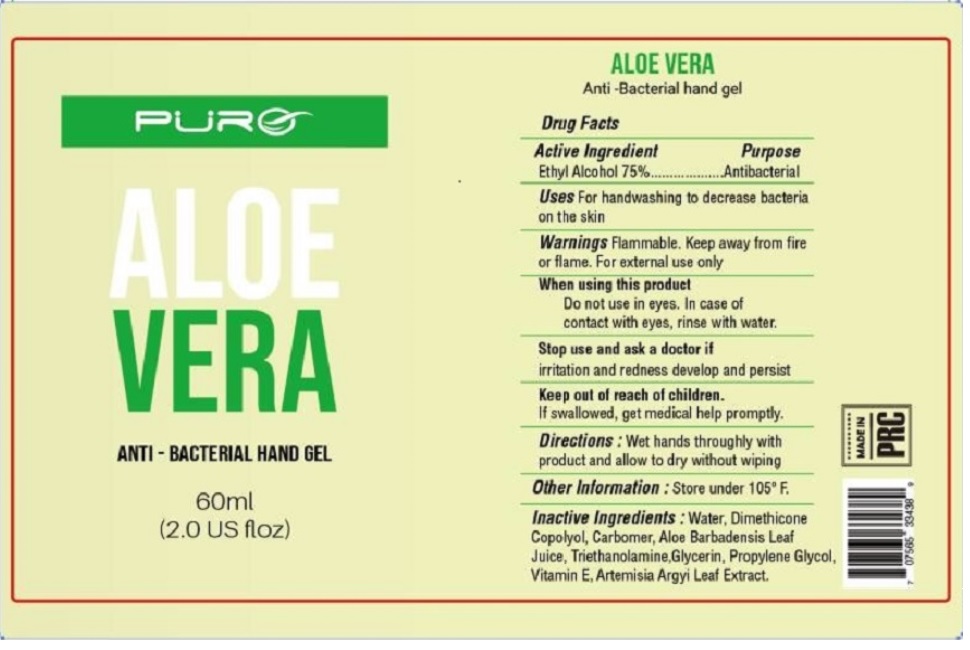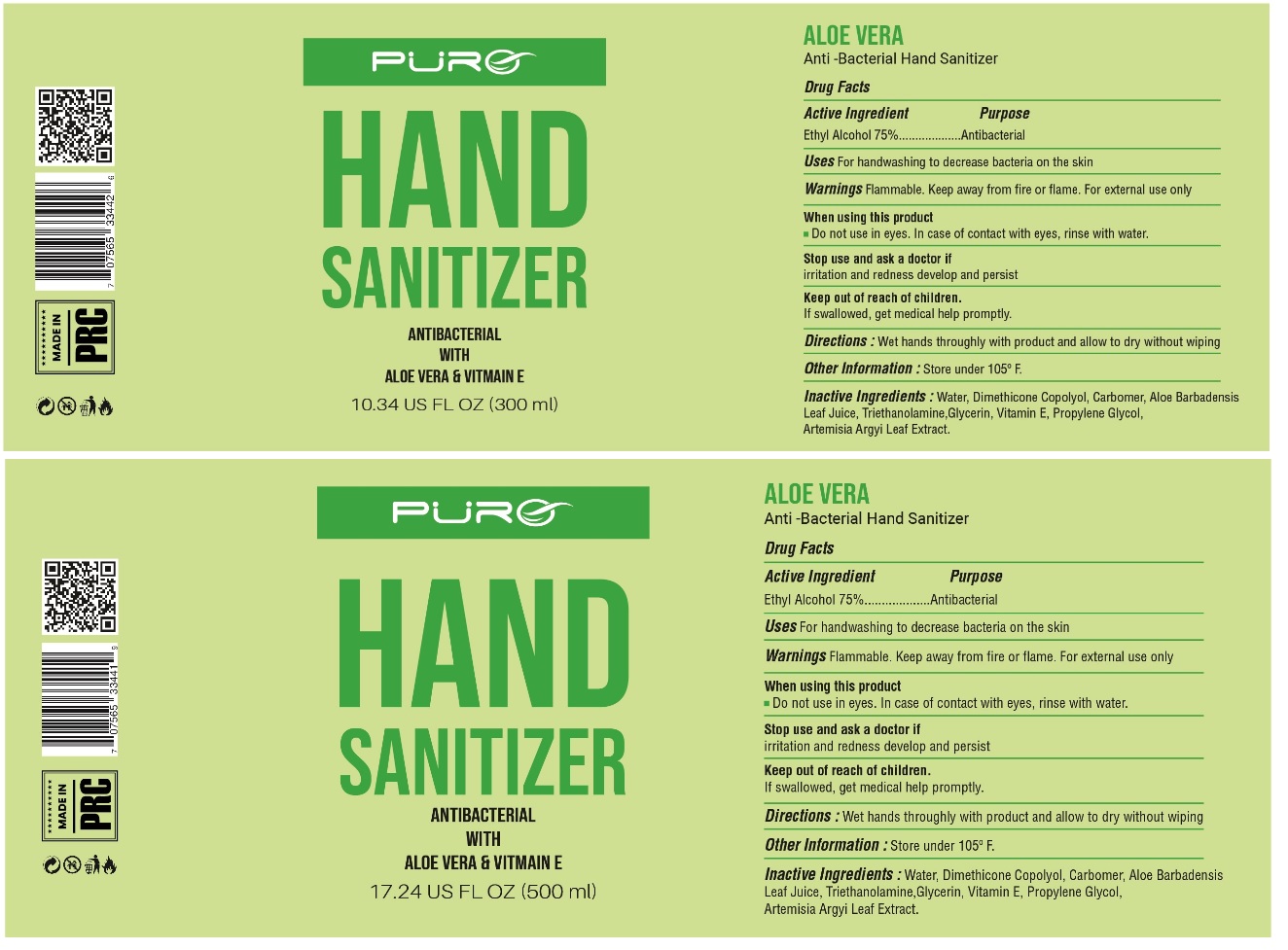 DRUG LABEL: PURO ALOE VERA ANTI-BACTERIAL HAND Gel
NDC: 74480-101 | Form: GEL
Manufacturer: PURE WHOLESALE LLC
Category: otc | Type: HUMAN OTC DRUG LABEL
Date: 20200605

ACTIVE INGREDIENTS: ALCOHOL 75 mL/100 mL
INACTIVE INGREDIENTS: WATER; PEG/PPG-18/18 DIMETHICONE; CARBOMER HOMOPOLYMER, UNSPECIFIED TYPE; ALOE VERA LEAF; TROLAMINE; GLYCERIN; PROPYLENE GLYCOL; .ALPHA.-TOCOPHEROL; ARTEMISIA ARGYI LEAF

PURO ALOE VERA ANTI - BACTERIAL HAND GEL

Active Ingredient

Ethyl Alcohol 75%

Purpose

Antibacterial

INDICATIONS AND USAGE

Uses For handwashing to decrease bacteria on the skin

WARNINGS

Warnings Flammable. Keep away from fire or flame. For external use only

When using this product

Do not use in eyes. In case of contact with eyes, rinse with water.

Stop use and ask a doctor if

irritation and redness develop and persist

Keep out of reach of children

If swallowed, get medical help promptly.

DOSAGE AND ADMINISTRATION

Directions : Wet hands thoroughly with product and allow to dry without wiping

Other information : Store under 105°F.

INACTIVE INGREDIENT

Inactive ingredients : Water, Dimethicone Copolyol, Carbomer, Aloe Barbadensis Leaf Juice, Triethanolamine, Glycerin, Propylene Glycol, Vitamin E, Artemisia Argyi Leaf Extract.

MADE IN PRC